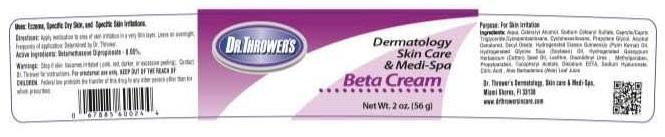 DRUG LABEL: DR. THROWERS BETA
NDC: 69299-201 | Form: CREAM
Manufacturer: DR. THROWER'S SKINCARE, INC.
Category: prescription | Type: HUMAN PRESCRIPTION DRUG LABEL
Date: 20150522

ACTIVE INGREDIENTS: BETAMETHASONE DIPROPIONATE 0.05 g/100 g
INACTIVE INGREDIENTS: WATER; CETOSTEARYL ALCOHOL; SODIUM CETOSTEARYL SULFATE; MEDIUM-CHAIN TRIGLYCERIDES; CYCLOMETHICONE 5; CYCLOMETHICONE 6; PROPYLENE GLYCOL; ALCOHOL; DECYL OLEATE; HYDROGENATED PALM KERNEL OIL; HYDROGENATED SOYBEAN OIL; HYDROGENATED COTTONSEED OIL; LECITHIN, SOYBEAN; DIAZOLIDINYL UREA; METHYLPARABEN; PROPYLPARABEN; .ALPHA.-TOCOPHEROL ACETATE; EDETATE DISODIUM; HYALURONATE SODIUM; ANHYDROUS CITRIC ACID; ALOE VERA LEAF

USES

ECZEMA, SPECIFIC DRY SKIN, AND SPECIFIC SKIN IRRITATIONS.

DIRECTIONS:

APPLY MEDICATION TO AREA OF SKIN IRRITATION IN A VERY THIN LAYER. LEAVE ON OVERNIGHT.

FREQUENCY OF APPLICATION: DETERMINED BY DR. THROWER.

INGREDIENTS:

AQUA, CETEARYL ALCOHOL, SODIUM CETEARYL SULFATE, CAPRYLIC/CAPRIC TRIGLYCERIDES, CYCLOPENTASILOXANE, CYCLOHEXASILOXANE, PROPYLENE GLYCOL, ALCOHOL DENATURED, DECYL OLEATE, HYDROGENATED ELAESIS GUINEENSIS (PALM KERNEL) OIL, HYDROGENATED GLYCINE SOYA (SOYBEAN) OIL, HYDROGENATED GOSSYPIUM HERBACEUM (COTTON) SEED OIL, LECITHIN, DIAZOLYDINYL UREA, METHYLPARABEN, PROPYLPARABEN, TOCOPHERYL ACETATE, DISODIUM EDTA, SODIUM HYALURONATE, CITRIC ACID, ALOE BARBADENSIS (ALOE) LEAF JUICE.

WARNINGS

STOP USE IF SKIN BECOMES IRRITATED (PINK, RED, DARKER, OR EXCESSIVE PEELING). CONTACT DR. THROWER FOR INSTRUCTIONS. FOR EXTERNAL USE ONLY. KEEP OUT OF REACH OF CHILDREN. FEDERAL LAW PROHIBITS THE TRANSFER OF THIS DRUG TO ANY OTHER PERSON OTHER THAN FOR WHOM PRESCRIBED.